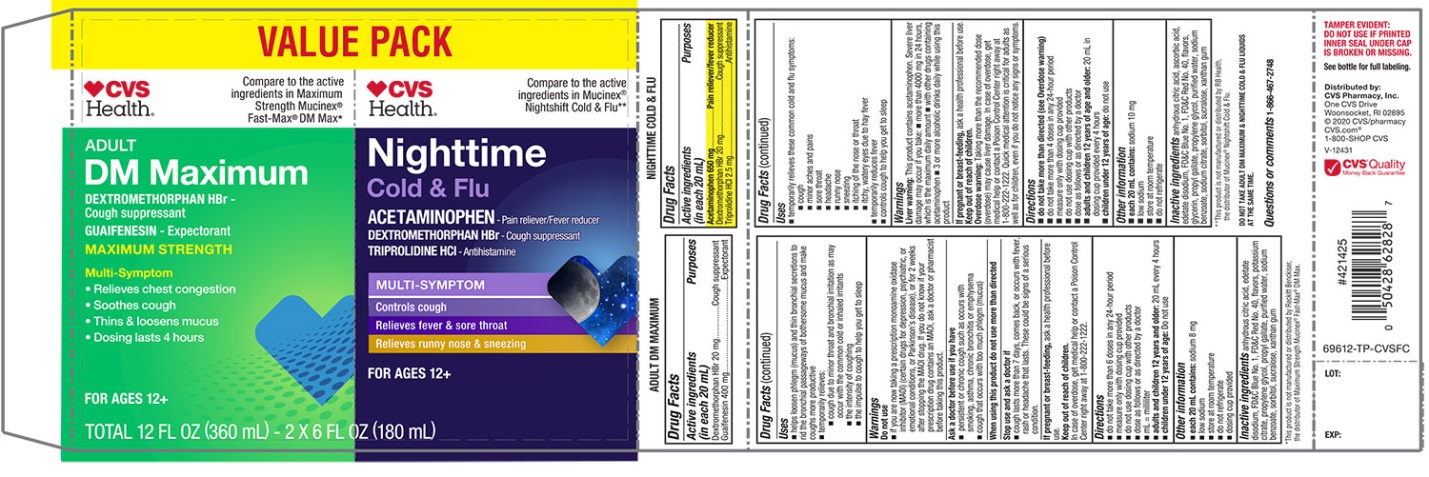 DRUG LABEL: CVS Mucus Relief DM and Overnight Cold and Flu
NDC: 69842-696 | Form: KIT | Route: ORAL
Manufacturer: CVS
Category: otc | Type: HUMAN OTC DRUG LABEL
Date: 20251209

ACTIVE INGREDIENTS: DEXTROMETHORPHAN HYDROBROMIDE 20 mg/20 mL; GUAIFENESIN 400 mg/20 mL; ACETAMINOPHEN 650 mg/20 mL; DEXTROMETHORPHAN HYDROBROMIDE 20 mg/20 mL; TRIPROLIDINE HYDROCHLORIDE 2.5 mg/20 mL
INACTIVE INGREDIENTS: ANHYDROUS CITRIC ACID; EDETATE DISODIUM; FD&C BLUE NO. 1; FD&C RED NO. 40; POTASSIUM CITRATE; PROPYLENE GLYCOL; PROPYL GALLATE; WATER; SODIUM BENZOATE; SORBITOL; SUCRALOSE; XANTHAN GUM; ANHYDROUS CITRIC ACID; EDETATE DISODIUM; FD&C BLUE NO. 1; FD&C RED NO. 40; GLYCERIN; PROPYL GALLATE; PROPYLENE GLYCOL; WATER; SODIUM BENZOATE; SODIUM CITRATE, UNSPECIFIED FORM; SORBITOL; SUCRALOSE; XANTHAN GUM

Maximum Strength Mucus Relief DM and Overnight Cold & Flu Value Pack

Drug Facts

ACTIVE INGREDIENT

PURPOSE

Active ingredients (in each 20 mL) Maximum Strength Mucus Relief DM Max | Purposes
Dextromethorphan HBr 20 mg | Cough suppressant
Guaifenesin 400 mg | Expectorant

Active ingredients (in each 20 mL) | Purposes
Nighttime Cold & Flu
Acetaminophen 650 mg | Pain reliever/fever reducer
Dextromethorphan HBr 20 mg | Cough suppressant
Triprolidine HCl 2.5 mg | Antihistamine

Uses

MAXIMUM STRENGTH MUCUS RELIEF DM

- helps loosen phlegm (mucus) and thin bronchial secretions to rid the bronchial passageways of bothersome mucus and make coughs more productive
- temporarily relieves
  - cough due to minor throat and bronchial irritation as may occur with the common cold or inhaled irritants
  - the intensity of coughing
  - the impulse to cough to help you get to sleep

Warnings

Do not use

- if you are now taking a prescription monoamine oxidase inhibitor (MAOI) (certain drugs for depression, psychiatric, or emotional conditions, or Parkinson's disease), or for 2 weeks after stopping the MAOI drug. If you do not know if your prescription drug contains an MAOI, ask a doctor or pharmacist before taking this product.

Ask a doctor before use if you have

- persistent or chronic cough such as occurs with smoking, asthma, chronic bronchitis or emphysema
- cough that occurs with too much phlegm (mucus)

When using this product do not use more that directed

Stop use and ask a doctor if

- cough lasts more than 7 days comes back or occurs with fever, rash or headache that lasts. These could be sings of a serious condition.

If pregnancy or breast-feeding, ask a health professional before use

Keep Out of Reach of Children

In case of overdose, get medical help or contact a Poison control Centre right away at 1-800-222-1222

Directions

- do not take more than 6 doses in any 24-hour period
- measure only with dosing cup provided
- do not use dosing cup with other products
- dose as follows or as directed by a doctor
- mL = milliliter
- adults and children 12 years and older:20 mL every 4 hours
- children under 12 years of age:Do not use

Other information

- each 20 mL contains:sodium 8 mg
- low sodium
- store at room temperature
- do not refrigerate
- dosing cup provided

Inactive ingredients (Maximum strength mucus relief DM)

anhydrous citric acid, edetate disodium, FD&C Blue No.1, FD&C Red No. 40, flavors, potassium citrate, propylene glycol, propyl gallate, purified water, sodium benzoate, sorbitol, sucralose, xanthan gum

Uses (Nighttime Cold and Flu)

- temporarily relieves these common cold and flu symptoms:
- cough
- minor aches and pains
- sore throat
- headache
- runny nose
- sneezing
- itching of the nose or throat
- itchy, watery eyes due to hay fever
- temporarily reduces fever
- controls cough to help you get to sleep

Warnings

Liver warnings:This product contains acetaminophen. Severe liver damage may occur if you take\

- more than 4000 mg in 24 hours, which is the maximum daily amount
- with other drugs containing acetaminophen
- 3 or more alcoholic drinks daily while using this product

If pregnant or breast feeding

Ask a health professional before use

Keep Out of Reach of Children

Overdose warning:Taking more than the recommended dose (overdose) may cause liver damage. In case of overdose, get medical help or contact a Poison Control Centre right away at 1-800-222-1222.

Quick medical attention is critical for adults as well as for children, even if you do not notice any signs

Directions

- do not take more than directed (see overdose warnings
- do not take more than 4 doses in any 24-hour period
- measure only with dosing cup provided
- do not use dosing cup with other products
- dose as follows or as directed by a doctor
- adults and children 12 years of age and older:20 ml in dosing cup provided every 4 hours
- children under 12 years of age:do not use

Other Information

- each 20 mL contains:sodium 10 mg
- low sodium
- store at room temperature
- do not refrigerate

Inactive ingredients (Overnight Cold & Flu)

anhydrous citric acid, ascorbic acid, edetate disodium, FD&C Blue No. 1, FD&C Red No. 40, flavors, glycerin, propyl gallate, propylene glycol, purified water, sodium benzoate, sodium citrate, sorbitol, sucralose, xanthan gum

Questions or comments?

(1-866-467-2748)

PRINCIPAL DISPLAY PANEL - Kit Carton

VALUE PACK

NDC 69842-696-12

Compare to the active ingredients Maximum Strength Mucinex® Fast Max® DM Max*

Mucus Relief DM

Dextromethorphan HBr • Cough Suppressant
Guaifenesin • Expectorant
MAXIMUM STRENGTH

MULTI-SYMPTOM

- Controls Cough
- Relieves chest congestion
- Thins & loosens mucus
- 4 hour dosing

For Ages 12+

*This product is not manufactured or distributed by Reckitt Benckiser, the distributor of Maximum Strength Mucinex® Fast-Max® DM Max.

Compare to Mucinex® Nightshift Cold & Flu Active Ingredients**

Overnight Cold & Flu

ACETAMINOPHEN• PAIN RELIEVER/FEVER REDUCER
DEXTROMETHORPHAN HBR • COUGH SUPPRESSANT

TRIPROLIDINE HCL • ANTIHISTAMINE

Night Time

Relief for Better Morning

Maximum Strength per 4-hour dose

- Cough
- Fever
- Sore Throat
- Runny Nose
- Sneezing

For Ages 12+

2 – 6 FL OZ (180 mL) BOTTLES / TOTAL 12 FL OZ (360 mL)

††These product is not manufactured or distributed by Reckitt Benckister Health, distributor of Maximum Strength Mucinex® Fast Max© DM Max & Mucinex© Nightshift Cold & Flu.

DO NOT TAKE ADULT DM MAXIMUM & NIGHTTIME COLD & FLU LIQUIDS AT THE SAME TIME.

TAMPER EVIDENT: DO NOT USE IF PRINTED INNER SEAL UNDER CAP IS BROKEN OR MISSING.;

See bottle for full labeling

Distributed By:

CVS Pharmacy, Inc.

One CVS Drive

Woonsocket, RI 02895

© 2020 CVS/pharmacy

CVS.com®

1-800-SHOP CVS

V-12431

CVS®Quality

Money Back Guarantee